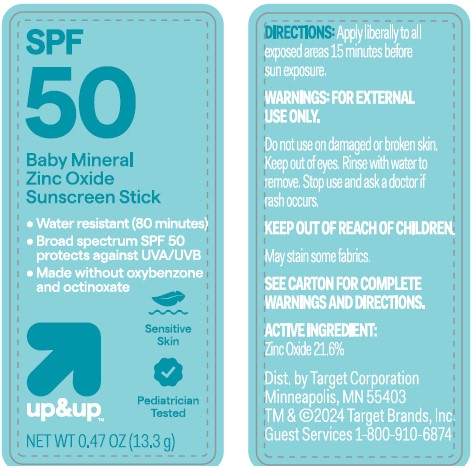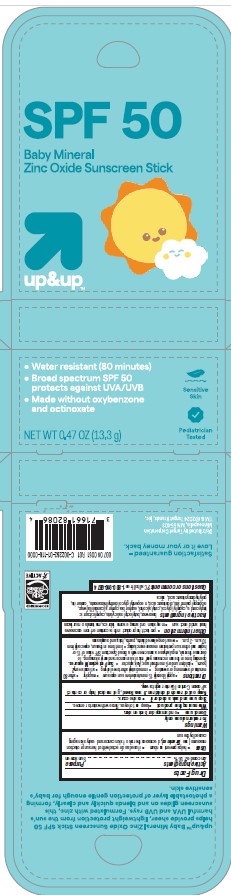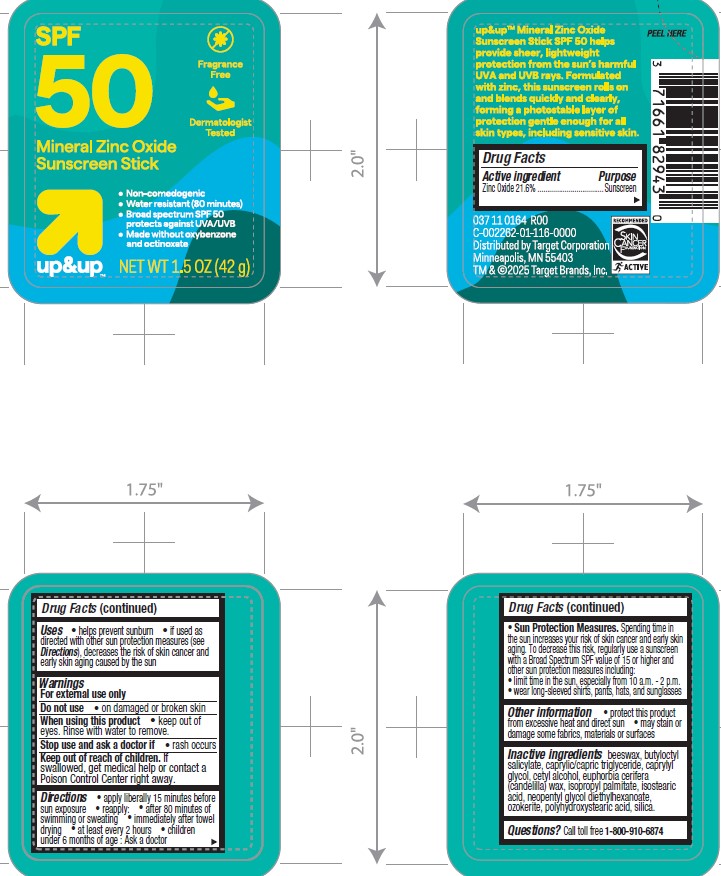 DRUG LABEL: Target Up and Up SPF 50 Mineral Zinc Oxide Sunscreen Stick
NDC: 82442-007 | Form: STICK
Manufacturer: TARGET CORPORATION
Category: otc | Type: HUMAN OTC DRUG LABEL
Date: 20240925

ACTIVE INGREDIENTS: ZINC OXIDE 216 mg/1 g
INACTIVE INGREDIENTS: POLYHYDROXYSTEARIC ACID (2300 MW); WHITE WAX; NEOPENTYL GLYCOL DIETHYLHEXANOATE; BUTYLOCTYL SALICYLATE; SILICON DIOXIDE; ISOPROPYL PALMITATE; MEDIUM-CHAIN TRIGLYCERIDES; CANDELILLA WAX; CAPRYLYL GLYCOL; CERESIN

Target Up and Up SPF 50 Mineral Zinc Oxide Sunscreen Stick

Active Ingredients

Zinc Oxide 21.6%

Purpose

Sunscreen

Uses

- helps prevent sunburn
- if used as directed with other sun protection measures (see Directions), decreases the risk of skin cancer and early skin aging caused by the sun

Warnings

For external use only

Do not use

• on damaged or broken skin.

When using this product

• keep out of eyes. Rinse with water to remove.

Stop use and ask a doctor if

• rash occurs.

Keep out of reach of children.

If swallowed, get medical help or contact a Poison Control Center right away.

Directions

- apply liberally 15 minutes before sun exposure
- reapply:

• after 80 minutes of swimming or sweating

• immediately after towel drying

• at least every 2 hours

- children under 6 months of age: Ask a doctor
- Sun Protection Measures. Spending time in the sun increases your risk of skin cancer and early skin aging. To decrease this risk, regularly use a sunscreen with a Broad Spectrum SPF value of 15 or higher and other sun protection measures including:

• limit time in the sun, especially from 10 a.m. - 2 p.m.

• wear long-sleeved shirts, pants, hats, and sunglasses

Other Information

- protect the product in this container from excessive heat and direct sun
- may stain or damage some fabrics, materials or surfaces

Inactive Ingredient(s)

beeswax, butyloctyl salicylate, caprylic/capric
triglyceride, caprylyl glycol, cetyl alcohol, euphorbia cerifera (candelilla) wax,
isopropyl palmitate, isostearic acid, neopentyl glycol diethylhexanoate, ozokerite,
polyhydroxystearic acid, silica